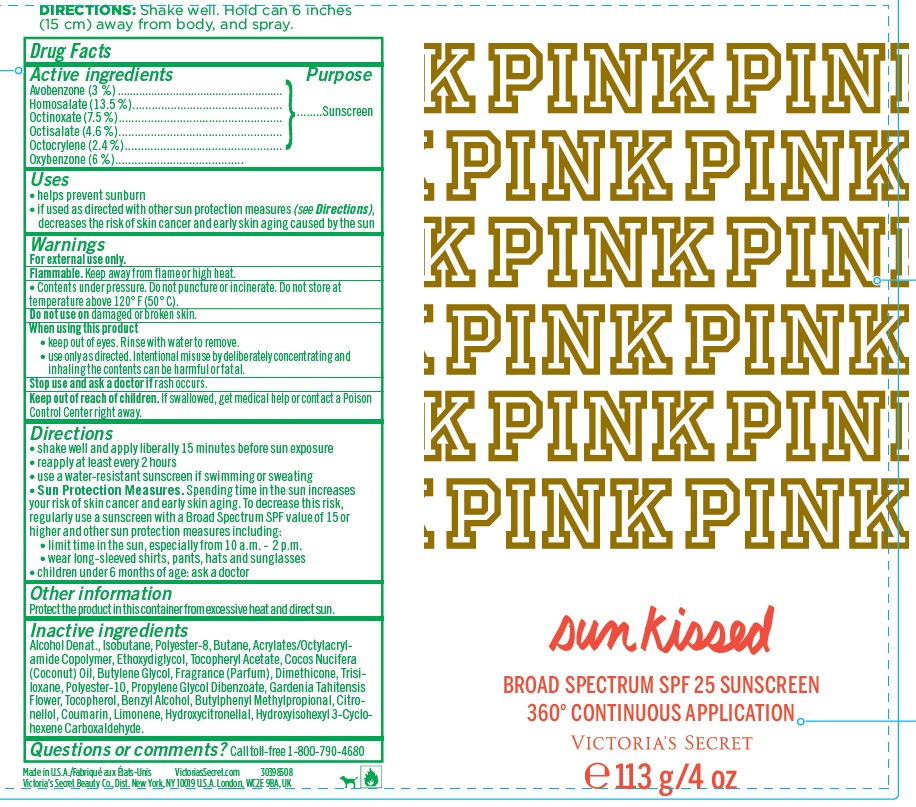 DRUG LABEL: Victorias Secret Pink Broad Spectrum SPF 25 Sunscreen Sunkissed
NDC: 62670-8049 | Form: AEROSOL, SPRAY
Manufacturer: Bath & Body Works, Inc.
Category: otc | Type: HUMAN OTC DRUG LABEL
Date: 20160411

ACTIVE INGREDIENTS: AVOBENZONE 3.0 mg/1 g; HOMOSALATE 13.5 mg/1 g; OCTINOXATE 7.5 mg/1 g; OCTISALATE 4.6 mg/1 g; OCTOCRYLENE 2.4 mg/1 g; OXYBENZONE 6.0 mg/1 g
INACTIVE INGREDIENTS: WATER

ACTIVE INGREDIENTS

Avobenzone 3.0%, Homosalate 13.5%, Octinoxate 7.5%, Octisalate 4.6%, Octocrylene 2.4%, Oxybenzone 6.0%

PURPOSE

Sunscreen

USES

- Helps prevent sunburn
- If used as directed with other sun protection measures (see Directions), decreases the risk of skin cancer and early skin aging caused by the sun

WARNINGS

For external use only.

FLAMMABLE

Keep away from flame or high heat.

- Contents under pressure. Do not puncture or incinerate. Do not store at temperatures above 120°F (50°C).

DO NOT USE

on damaged or broken skin.

WHEN USING THIS PRODUCT

- keep out of eyes. Rinse with water to remove.
- use only as directed. Intentional misuse by deliberately concentrating and inhaling the contents can be harmful or fatal.

STOP USE AND ASK A DOCTOR IF

rash occurs.

KEEP OUT OF REACH OF CHILDREN.

If swallowed, get medical help or contact a Poison Control Center right away.

DIRECTIONS

- shake well and apply liberally 15 minutes before sun exposure
- reapply at least every 2 hours
- use a water-resistant sunscreen if swimming or sweating
- Sun Protection Measures. Spending time in the sun increases your risk of skin cancer and early skin aging. To decrease this risk, regularly use a sunscreen with a Broad Spectrum SPF value of 15 or higher and other sun protection measures including:
- limit time in the sun, especially from 10 a.m. - 2 p.m.
- wear long-sleeved shirts, pants, hats and sunglasses
- children under 6 months of age: ask a doctor

OTHER INFORMATION

Protect the product in this container from excessive heat and direct sun.

INACTIVE INGREDIENTS

Alcohol Denat., Isobutane, Polyester-8, Butane, Acrylates/Octylacrylamide Copolymer, Ethoxydiglycol, Tocopheryl Acetate, Cocos Nucifera
(Coconut) Oil, Butylene Glycol, Fragrance (Parfum), Dimethicone, Trisiloxane, Polyester-10, Propylene Glycol Dibenzoate, Gardenia Tahitensis
Flower, Tocopherol, Benzyl Alcohol, Butylphenyl Methylpropional, Citronellol, Coumarin, Limonene, Hydroxycitronellal, Hydroxyisohexyl 3-Cyclohexene Carboxaldehyde.

COMPANY INFORMATION

Victoria's Secret Beauty Co., Dist

New York, NY 10019 U.S.A.

London, WC2E 9BA, UK